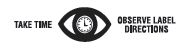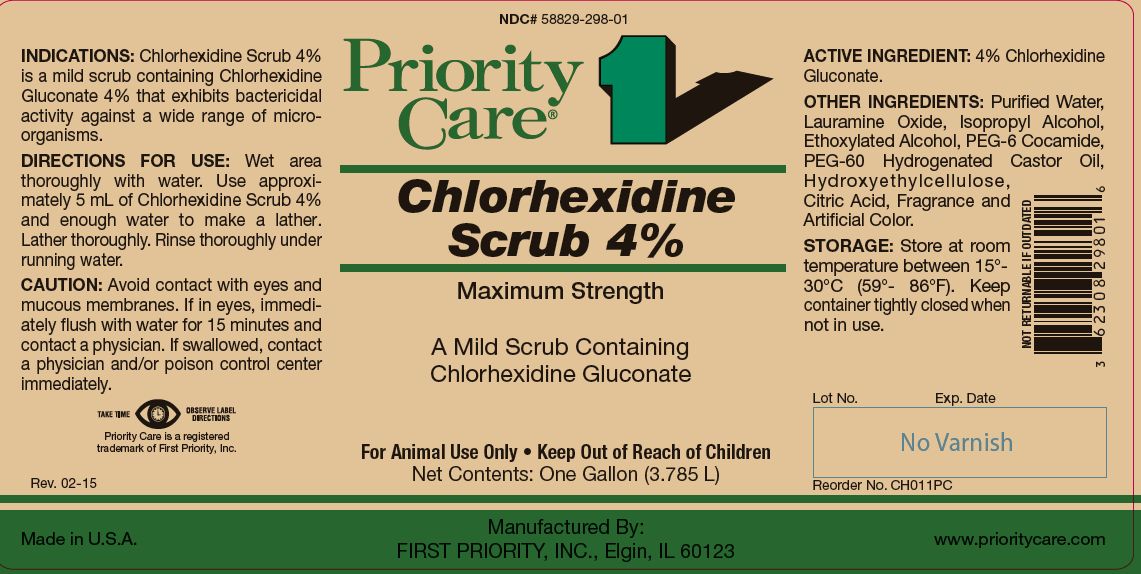 DRUG LABEL: Chlorhexidine Scrub
NDC: 58829-298 | Form: LIQUID
Manufacturer: FIRST PRIORITY INCORPORATED
Category: animal | Type: OTC ANIMAL DRUG LABEL
Date: 20221110

ACTIVE INGREDIENTS: CHLORHEXIDINE GLUCONATE 214.5 g/1 L

Chlorhexidine Scrub 4%

PURPOSE

Maximum Strength

A Mild Scrub Containing Chlorhexidine Gluconate

KEEP OUT OF REACH OF CHILDREN

For Animal Use Only • Keep Out of Reach of Children

INDICATIONS:

Chlorhexidine Scrub 4% is a mild scrub containing Chlorhexidine Gluconate 4% that exhibits bactericidal activity against a wide range of microorganisms.

DIRECTIONS FOR USE:

Wet area thoroughly with water. Use approximately 5 mL of Chlorhexidine Scrub 4% and enough water to make a lather. Lather thoroughly. Rinse thoroughly under running water.

CAUTION:

Avoid contact with eyes and mucous membranes. If in eyes, immediately flush with water for 15 minutes and contact a physician. If swallowed, contact a physician and/or poison control center immediately.

ACTIVE INGREDIENT:

4% Chlorhexidine Gluconate.

OTHER INGREDIENTS:

Purified Water, Lauramine Oxide, Isopropyl Alcohol, Ethoxylated Alcohol, PEG-6 Cocamide, PEG-60 Hydrogenated Castor Oil, Hydroxyethylcellulose, Citric Acid, Fragrance and Artificial Color.

STORAGE:

Store at room temperature between 15°- 30°C (59°- 86°F). Keep container tightly closed when not in use.

Net Contents:

One Gallon (3.785 L) Reorder No. CH011PC

INFORMATION FOR OWNERS/CAREGIVERS

Priority Care is a registered trademark of First Priority, Inc.

Made in U.S.A.

Manufactured By: FIRST PRIORITY, INC., Elgin, IL 60123

www.prioritycare.com